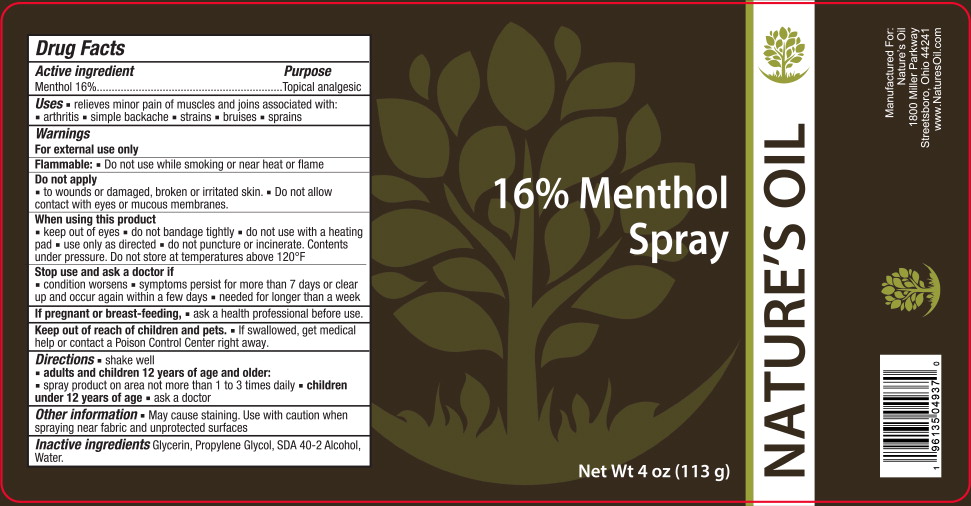 DRUG LABEL: Natures Oil 16% Menthol
NDC: 66902-242 | Form: SPRAY
Manufacturer: NATURAL ESSENTIALS, INC.
Category: otc | Type: HUMAN OTC DRUG LABEL
Date: 20240214

ACTIVE INGREDIENTS: MENTHOL, UNSPECIFIED FORM 160 mg/1 g
INACTIVE INGREDIENTS: ALCOHOL; GLYCERIN; PROPYLENE GLYCOL; WATER

Drug Facts

Active ingredient

Menthol 16%

Purpose

Topical analgesic

Uses

- relieves minor pain of muscles and joins associated with:
  - arthritis
  - simple backache
  - strains
  - bruises
  - sprains

Warnings

For external use only

Flammable:

- Do not use while smoking or near heat or flame

Do not apply

- to wounds or damaged, broken or irritated skin. - Do not allow contact with eyes or mucous membranes.

When using this product

- keep out of eyes
- do not bandage tightly
- do not use with a heating pad
- use only as directed
- do not puncture or incinerate. Contents under pressure. Do not store at temperatures above 120°F

Stop use and ask a doctor if

- condition worsens
- symptoms persist for more than 7 days or clear up and occur again within a few days
- needed for longer than a week

If pregnant or breast-feeding,

- ask a health professional before use.

Keep out of reach of children and pets.

- If swallowed, get medical help or contact a Poison Control Center right away.

Directions

- shake well

- adults and children 12 years of age and older:
  - spray product on area not more than 1 to 3 times daily
- children under 12 years of age
  - ask a doctor

Other information

- May cause staining. Use with caution when spraying near fabric and unprotected surfaces

Inactive ingredients

Glycerin, Propylene Glycol, SDA 40-2 Alcohol, Water.

Principal Display Panel - 118 g Can Label

NATURE'S OIL

16% Menthol
Spray

Net Wt 4 oz (113g)

Manufactured For:

Nature's Oil

1800 Miller Parkway
Streetsboro, Ohio 44241

www.NaturesOil.com